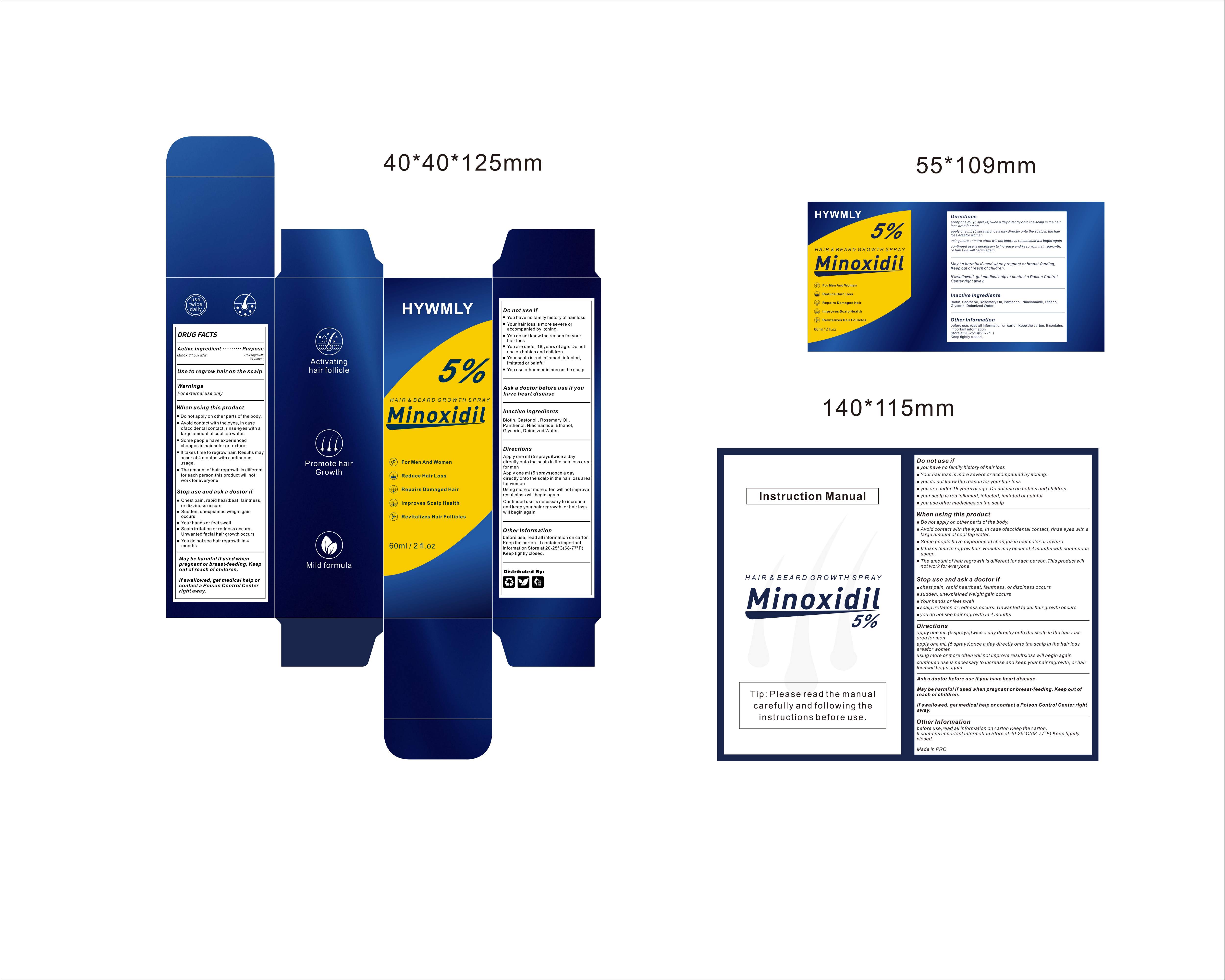 DRUG LABEL: 5%MinoxidilHairgrowthSpray
NDC: 84778-109 | Form: SHAMPOO
Manufacturer: Guangzhou Yixin Cross-border E-commerce Co., Ltd.
Category: otc | Type: HUMAN OTC DRUG LABEL
Date: 20251030

ACTIVE INGREDIENTS: MINOXIDIL 5 mg/100 mL
INACTIVE INGREDIENTS: WATER; NIACINAMIDE; PANTHENOL; BIOTIN; CASTOR OIL; GLYCERIN; ACETALDEHYDE; ROSEMARY OIL

Active ingredients

Minoxidil 5% Hair regrowth treatment

Uses

to regrow hair on the scalp
to help reverse hereditary hair loss

Purpose

to regrow hair on the scalp
to help reverse hereditary hair loss

Warnings

For external use only.

Flammable: Keep away from fire or flame

Dosage and administration

For external use only.

Do not use

you have no family history of hair loss

your hairloss is sudden and/or patchy

you do not know the reason for your hair loss

you are under 18 years of age.

Do not use on babies and children.

your scalp is red, inflamed,infected, irritated, or painfulyou use other medicines on the scalp

When using section

do not apply on other parts of the body

avoid contact with the eyes. in case of accidental contact, rinse eyes with large amountsof cool tap water.

some people have experienced changes in hair color and/or texture

it takes time to regrow hair. Results may occur at 2 months with twice a day usage. For somemen, you mav need to use this product for at least 4 months before vou see results.

the amount of hair regrowth is diferent for each person. This product will not work for all men.

stop use

chest pain, rapid heartbeat, faintness, or dizziness occurs

sudden.unexplained weight gain occurs

your hands or feet swell

scalo irritation or redness occurs

unwanted facial hair growth occurs

you do not see hair regrowth in 4 months

Keep out of reach of children.lf swallowed, get medical help or contacta Poison Control Center right away.

Inactive ingredients

Biotin, Castor oil, Rosemary Oil, Panthenol,Niacinamide,Ethanol,Glycerin,Deionized Water